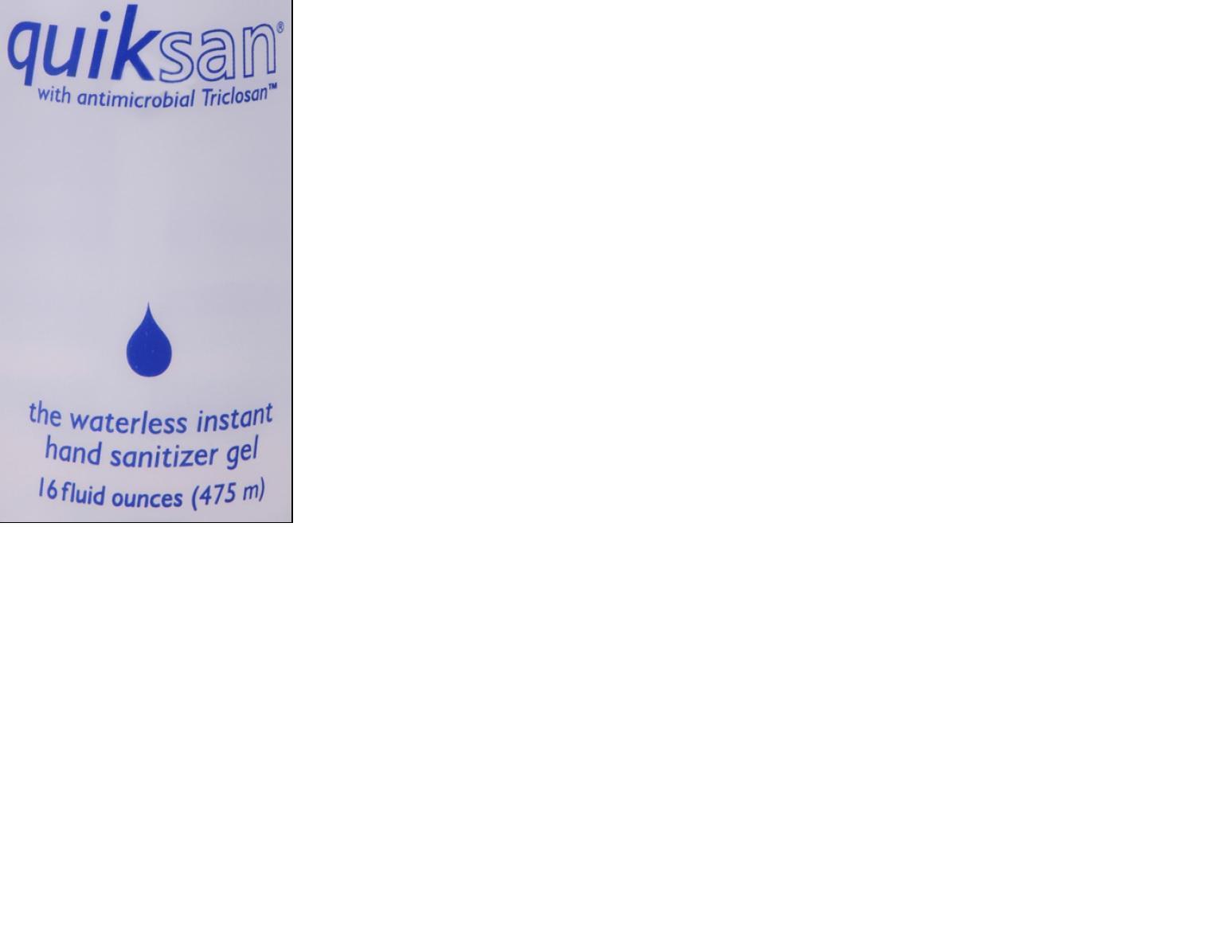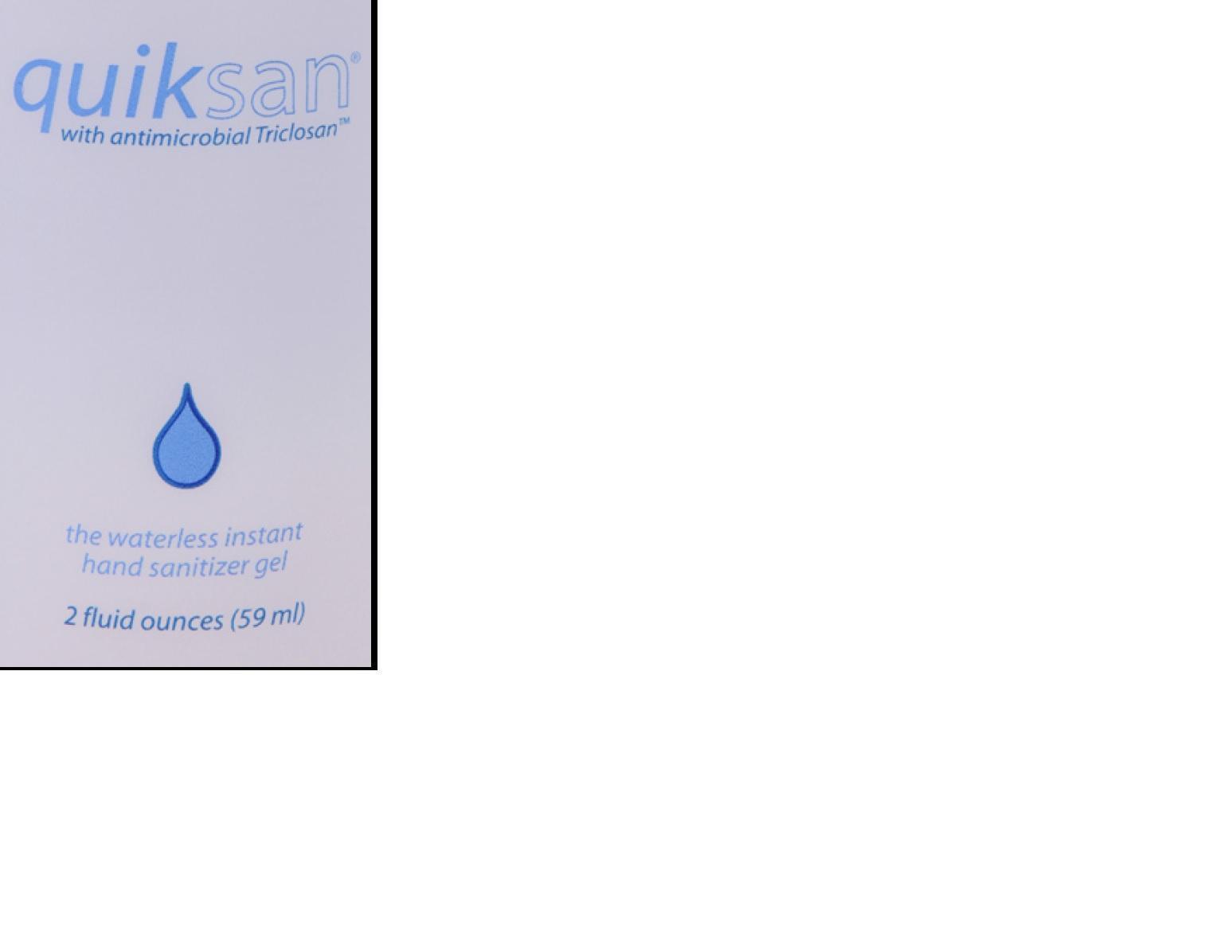 DRUG LABEL: Quiksan
NDC: 25113-111 | Form: SOLUTION
Manufacturer: The Dodge Company Inc
Category: otc | Type: HUMAN OTC DRUG LABEL
Date: 20140427

ACTIVE INGREDIENTS: TRICLOSAN 0.00025 g/1 g
INACTIVE INGREDIENTS: ISOPROPYL ALCOHOL; WATER; HYDROXYPROPYL CELLULOSE

Quiksan

WARNINGS SECTION

1) KEEP AWAY FROM HEAT, SPARKS, OR FLAME.

2) For external use only.

3) Do not use in the eyes. In case of contact, flush with water for 15 minutes.

4) Discontinue use if irritation and redness develop. If condition persists for more than 72 hours consult a doctor.

OTC - PURPOSE SECTION

Antiseptic handwash

INDICATIONS & USAGE SECTION

Antiseptic handwash for handwashing to decrease baceria on the skin

DOSAGE & ADMINISTRATION SECTION

Apply a small amount to dry hands. Rub hands together coating entire surface of hands. Quiksan will disapear in about 15 seconds.

OTC - KEEP OUT OF REACH OF CHILDREN SECTION

Keep out of reach of children. If swallowed, get medical help or contact a Poison Control Center right away.

OTC - ACTIVE INGREDIENT SECTION

Triclosan

ACKAGE LABEL.PRINCIPAL DISPLAY PANEL

Quiksan 2oz.jpg

PACKAGE LABEL.PRINCIPAL DISPLAY P

Quiksan 16oz.jpg